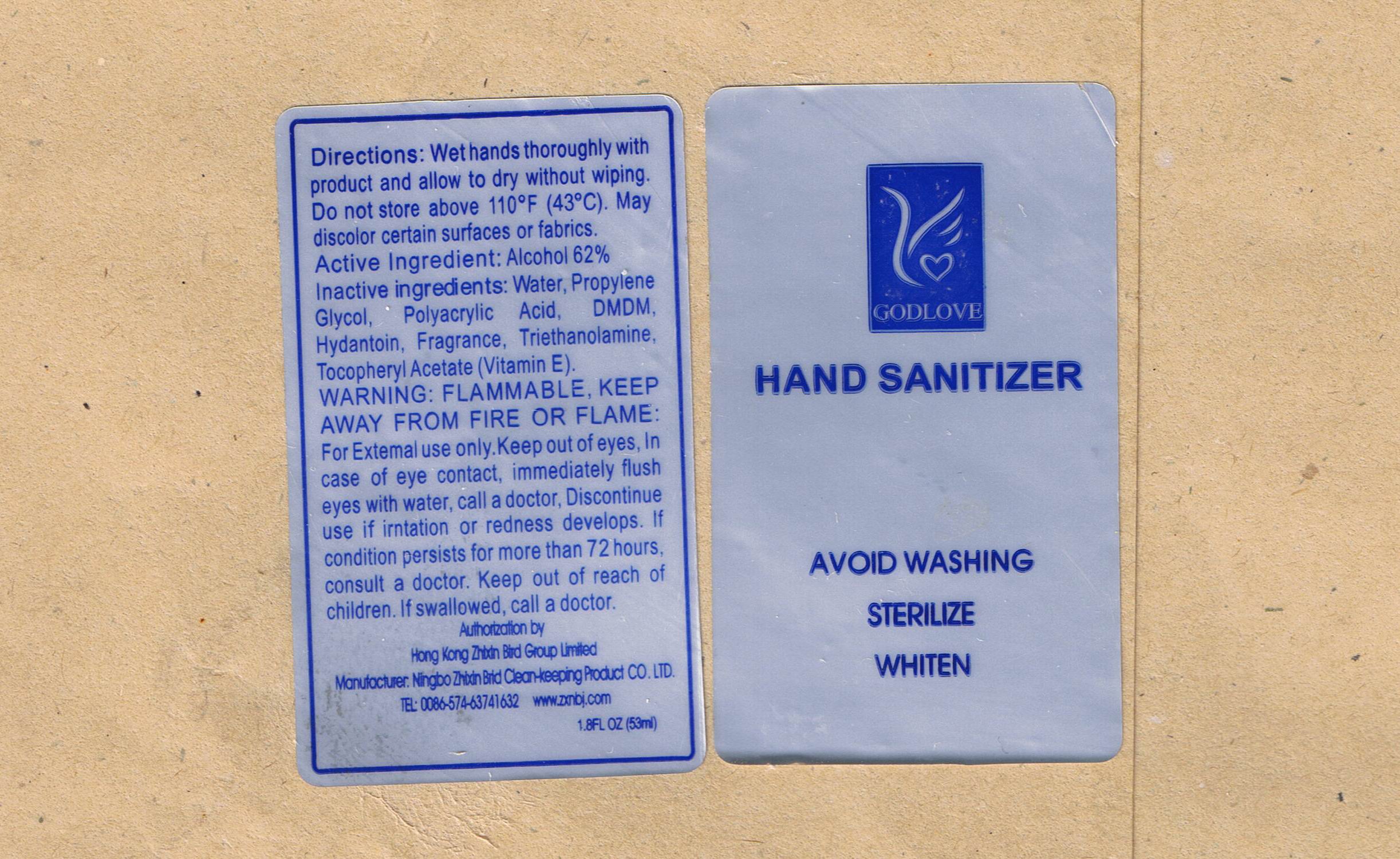 DRUG LABEL: Goldlove Hand Sanitizer
NDC: 49877-006 | Form: LIQUID
Manufacturer: Cixi Zhixin Bird Clean-care Product Co., Ltd.
Category: otc | Type: HUMAN OTC DRUG LABEL
Date: 20091110

ACTIVE INGREDIENTS: ALCOHOL 62 g/100 g
INACTIVE INGREDIENTS: WATER 37.809 g/100 g; TROLAMINE 0.02 g/100 g; ALPHA-TOCOPHEROL 0.001 g/100 g; PROPYLENE GLYCOL 0.1 g/100 g; 1,3-DIMETHYLOL-5,5-DIMETHYL-HYDANTOIN 0.02 g/100 g; CARBOMER HOMOPOLYMER TYPE C 0.02 g/100 g

Goldlove Hand Sanitizer

DOSAGE AND ADMINISTRATION

Directions: Wet hands thoroughly with product and allow to dry without wiping

STORAGE AND HANDLING

Do not store above 110F (43C). May discolor certain surfaces and fabrics.

Active Ingredient: Alcohol 62%

INACTIVE INGREDIENT

Inactive Ingredients: Water, Propylene Glycol, Polyacrylic Acid, DMDM Hydantoin, Fragrance, Triethanolamine, Tocopheryl Acetate (Vitamin E)

WARNINGS AND PRECAUTIONS

WARNING: FLAMMABLE, KEEP AWAY FROM FIRE OR FLAME.

GENERAL PRECAUTIONS

For external use only. Keep out of eye, in case of eye contact, immediately flush eyes with water, call a doctor. Discontinue use if irritation or redness develops. If condition persists for more than 72 hours, consult a doctor. Keep out of reach of children. If swallowed, call a doctor.

label